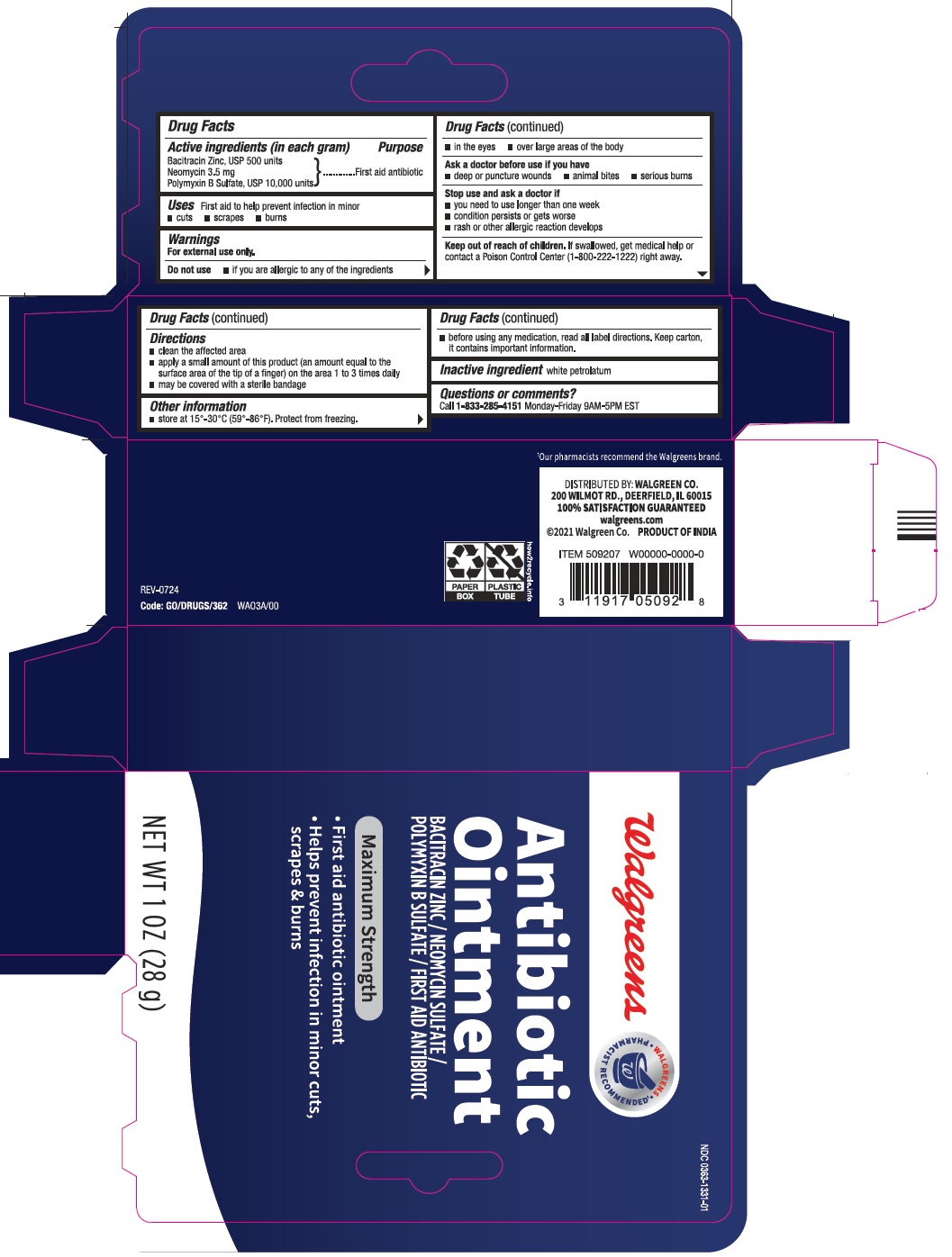 DRUG LABEL: ANTIBIOTIC
NDC: 0363-1331 | Form: OINTMENT
Manufacturer: Walgreens Co.
Category: otc | Type: Human OTC Drug Label
Date: 20250129

ACTIVE INGREDIENTS: BACITRACIN ZINC 500 [iU]/1 g; NEOMYCIN SULFATE 3.5 mg/1 g; POLYMYXIN B SULFATE 10000 [iU]/1 g
INACTIVE INGREDIENTS: WHITE PETROLATUM

Antibiotic Ointment (Bacitracin Zinc, Neomycin Sulfate, Polymyxin B Sulfate)

ACTIVE INGREDIENT(S)

Active Ingredient (in each gram)

Bacitracin Zinc, USP 500 units

Neomycin 3.5mg

Polymyxin B Sulfate, USP 10,000 units

PURPOSE

First aid antibiotic

USE(S)

First aid to help prevent infection in minor

- cuts
- scrapes
- burns

WARNINGS

For external use only.

DO NOT USE

- if you are allergic to any of the ingredients
- in the eyes
- over large areas of the body

ASK A DOCTOR BEFORE USE IF YOU HAVE

■ deep or puncture wounds

■ animal bites

■ serious burns

STOP USE AND ASK A DOCTOR IF

■ you need to use longer than one week

■ condition persists or gets worse

■ rash or other allergic reaction develops

KEEP OUT OF REACH OF CHILDREN

If swallowed, get medical help or contact a Poison Control Center (1-800-222-1222) right away.

DIRECTIONS

■ clean the affected area
■ apply a small amount of this product (an amount equal to the surface area of the tip of a finger) on the area 1 to 3 times daily
■ may be covered with a sterile bandage

OTHER INFORMATION

■ store at 15°-30°C (59°-86°F). Protect from freezing.

■ before using any medication, read all label directions. Keep carton, it contains important information.

INACTIVE INGREDIENT

white petrolatum

QUESTIONS OR COMMENTS?

Call 1-833-285-4151 Monday-Friday 9AM-5PM EST